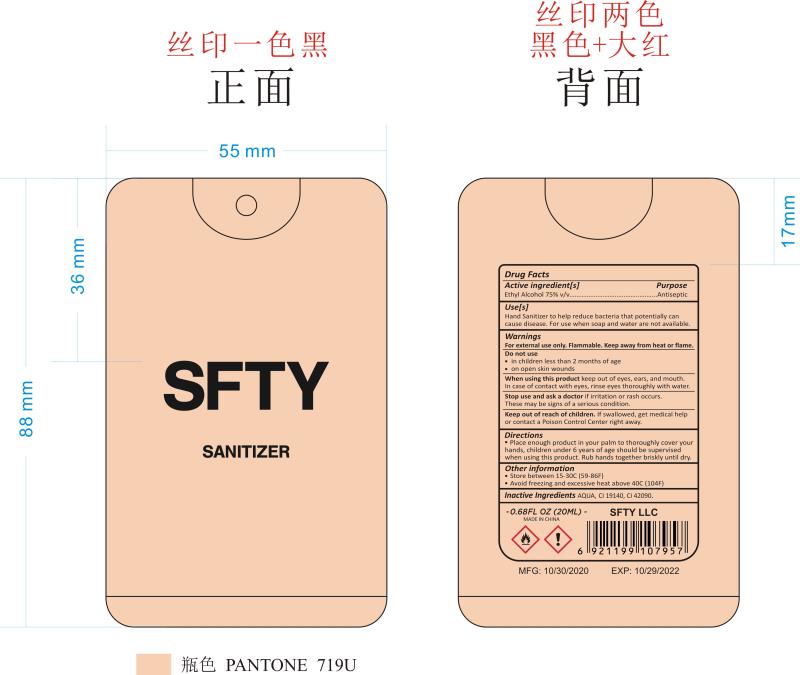 DRUG LABEL: sfty sanitizer
NDC: 74913-560 | Form: LIQUID
Manufacturer: SHANTOU S.E.Z BAOJIE INDUSTRY CO., LTD
Category: otc | Type: HUMAN OTC DRUG LABEL
Date: 20201126

ACTIVE INGREDIENTS: ALCOHOL 75 mL/100 mL
INACTIVE INGREDIENTS: WATER 25 mL/100 mL

sfty sanitizer

Active Ingredient(s)

Alcohol 75% v/v. Purpose: Antiseptic

Purpose

Antiseptic, Alcohol Cleaning Spray

Use

hand sanitizer to help reduce bacteria that protentialy can cause disease. for use when soap and water are aviaiable

Warnings

For external use only. Flammable. Keep away from heat or flame

Do not use

- in children less than 2 months of age
- on open skin wounds

When using this product keep out of eyes, ears, and mouth. In case of contact with eyes, rinse eyes thoroughly with water.

Stop use and ask a doctor if irritation or rash occurs. These may be signs of a serious condition.

Keep out of reach of children. If swallowed, get medical help or contact a Poison Control Center right away.

Inactive ingredients

Water